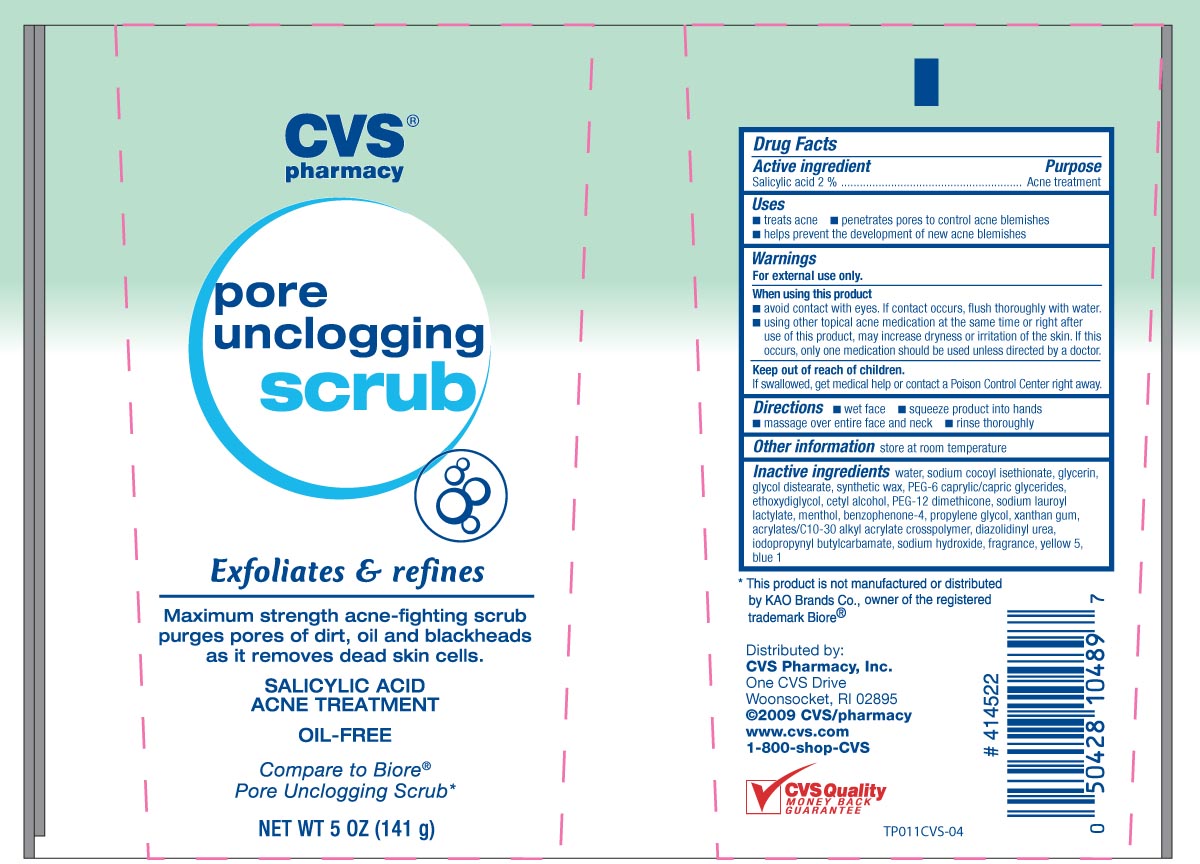 DRUG LABEL: CVS Pore Unclogging Scrub
NDC: 59779-812 | Form: SOAP
Manufacturer: CVS Pharmacy
Category: otc | Type: HUMAN OTC DRUG LABEL
Date: 20100708

ACTIVE INGREDIENTS: SALICYLIC ACID 20 mg/1 g
INACTIVE INGREDIENTS: WATER; AVOBENZONE; GLYCERIN; XANTHAN GUM; TRIHYDROXYSTEARIN; GLYCOL DISTEARATE; ISODECETH-6; DIETHYLENE GLYCOL MONOETHYL ETHER; CETYL ALCOHOL; TRISILOXANE; SODIUM ISOSTEAROYL LACTYLATE; SODIUM COCOYL ISETHIONATE; DIAZOLIDINYL UREA; IODOPROPYNYL BUTYLCARBAMATE; MENTHOL; PROPYLENE GLYCOL; FD&C BLUE NO. 1; FD&C YELLOW NO. 5; MICROCRYSTALLINE WAX; SODIUM HYDROXIDE

DRUG FACTS

Active ingredient Purpose
Salicylic Acid 2%.........................................Acne treatment

Uses
- treats acne - penetrates pores to control acne blemishes
- helps prevent the development of new acne blemishes

Keep out of reach of children. If swallowed, get medical help or contact a
Poison Control Center right away.

Uses
- treats acne - penetrates pores to control acne blemishes
- helps prevent the development of new acne blemishes

Warnings
For external use only
Flammable, Keep away from fire or flame
When using this product
- avoid contact with eyes. If contact occurs, flush thoroughly with water.
- using other topical acne medications at the same time or right after use of this product,
may increase dryness or irritation of the skin. If this occurs, only one medication should
be used unless directed by a doctor.
Keep out of reach of children.If swallowed, get medical help or contact a
Poison Control Center right away.

Directions
- wet face - squeeze product onto hands
- massage over face and neck - rinse thoroughly
Other information store at room temperature

Inactive Ingredients
water, sodium cocoyl isethionate, glycerin, glycol distearate, synthetic wax,
PEG-6 caprylic/capric clycerides, ethoxydiglycol, cetyl alcohol, PEG-12 dimethicone,
sodium lauroyl lactylate, menthol, benzophenone-4, propylene glycol, xanthan gum,
acrylates/c 10-30 alkyl acrylate crosspolymer, diazolidinyl urea, iodopropynyl butylcarbamate,
sodium hydroxide, fragrance, yellow 5, blue 1